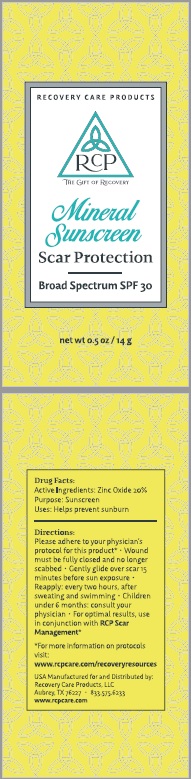 DRUG LABEL: SUNSCREEN
NDC: 62932-188 | Form: OINTMENT
Manufacturer: Private Label Select Ltd CO
Category: otc | Type: HUMAN OTC DRUG LABEL
Date: 20181130

ACTIVE INGREDIENTS: ZINC OXIDE 25 g/100 g
INACTIVE INGREDIENTS: CARNAUBA WAX; HELIANTHUS ANNUUS SEED WAX; TOCOPHEROL; YELLOW WAX; CASTOR OIL; SHEA BUTTER; ALOE VERA LEAF; COCONUT OIL; CANDELILLA WAX; COCOA BUTTER

RCP Mineral Sunscreen SPF30